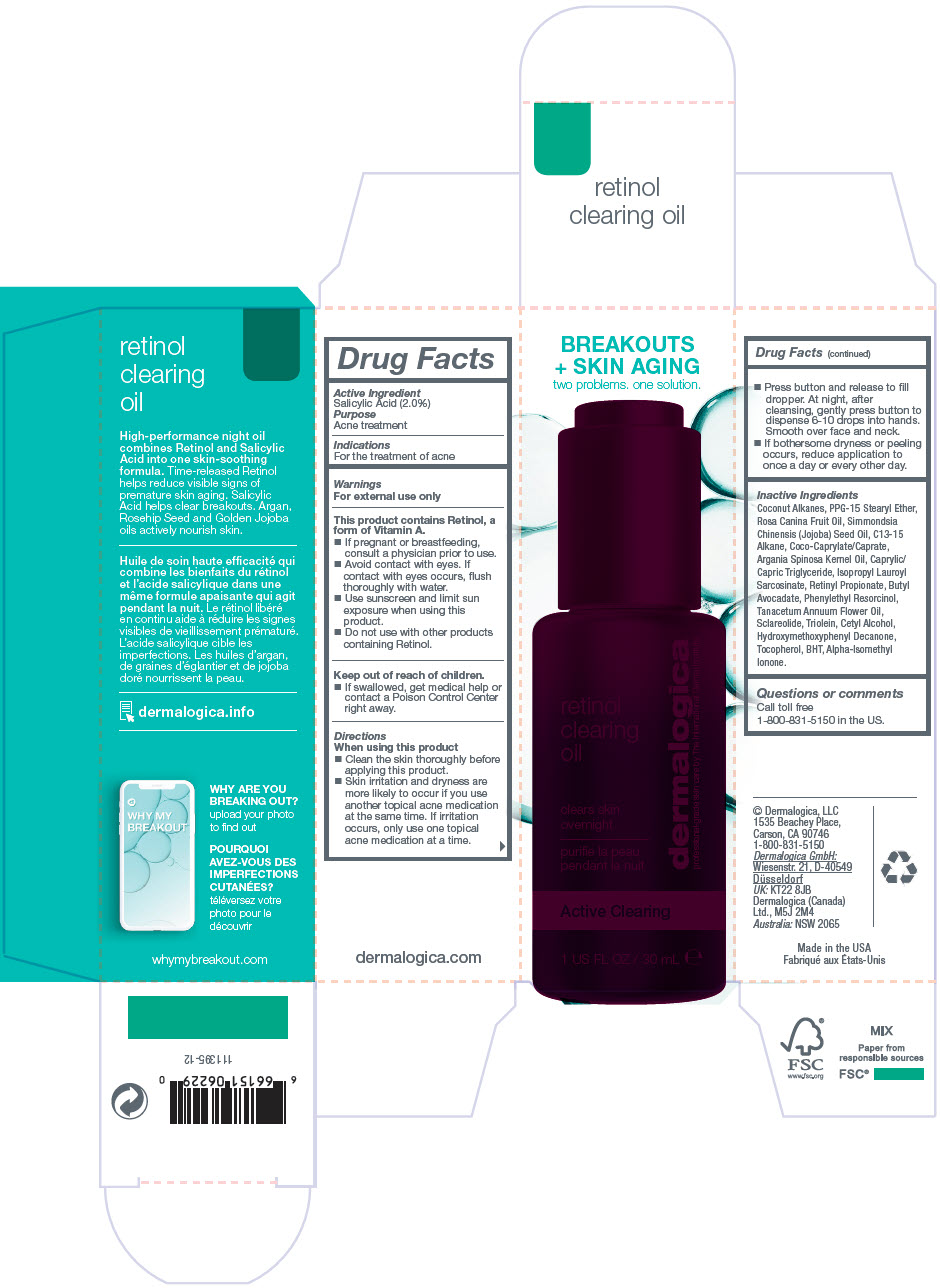 DRUG LABEL: RETINOL CLEARING
NDC: 68479-141 | Form: OIL
Manufacturer: Dermalogica, LLC.
Category: otc | Type: HUMAN OTC DRUG LABEL
Date: 20241230

ACTIVE INGREDIENTS: Salicylic Acid 2 mg/100 mL
INACTIVE INGREDIENTS: Coconut Alkanes; POLYPROPYLENE GLYCOL 15 STEARYL ETHER; ROSA CANINA FRUIT OIL; JOJOBA OIL; C13-15 Alkane; COCOYL CAPRYLOCAPRATE; ARGAN OIL; MEDIUM-CHAIN TRIGLYCERIDES; Isopropyl Lauroyl Sarcosinate; GLYCERYL TRIOLEATE; Butyl Avocadate; Cetyl Alcohol; Retinyl Propionate; Phenylethyl Resorcinol; Sclareolide; TANACETUM ANNUUM FLOWERING TOP OIL; 1-(4-HYDROXY-3-METHOXYPHENYL)-DECAN-3-ONE; BUTYLATED HYDROXYTOLUENE; Tocopherol; ISOMETHYL-.ALPHA.-IONONE

RETINOL CLEARING OIL

Drug Facts

Active Ingredient

Salicylic Acid (2.0%)

Purpose

Acne treatment

Indications

For the treatment of acne

Warnings

For external use only

This product contains Retinol, a form of Vitamin A.

- If pregnant or breastfeeding, consult a physician prior to use.
- Avoid contact with eyes. If contact with eyes occurs, flush thoroughly with water.
- Use sunscreen and limit sun exposure when using this product.
- Do not use with other products containing Retinol.

Keep out of reach of children.

- If swallowed, get medical help or contact a Poison Control Center right away.

Directions

When using this product

- Clean the skin thoroughly before applying this product.
- Skin irritation and dryness are more likely to occur if you use another topical acne medication at the same time. If irritation occurs, only use one topical acne medication at a time.
- Press button and release to fill dropper. At night, after cleansing, gently press button to dispense 6-10 drops into hands. Smooth over face and neck.
- If bothersome dryness or peeling occurs, reduce application to once a day or every other day.

Inactive Ingredients

Coconut Alkanes, PPG-15 Stearyl Ether, Rosa Canina Fruit Oil, Simmondsia Chinensis (Jojoba) Seed Oil, C13-15 Alkane, Coco-Caprylate/Caprate, Argania Spinosa Kernel Oil, Caprylic/ Capric Triglyceride, Isopropyl Lauroyl Sarcosinate, Retinyl Propionate, Butyl Avocadate, Phenylethyl Resorcinol, Tanacetum Annuum Flower Oil, Sclareolide, Triolein, Cetyl Alcohol, Hydroxymethoxyphenyl Decanone, Tocopherol, BHT, Alpha-Isomethyl Ionone.

Questions or comments

Call toll free 1-800-831-5150 in the US.

PRINCIPAL DISPLAY PANEL - 30 mL Bottle Carton

BREAKOUTS
+ SKIN AGING
two problems. one solution.

retinol
clearing
oil

clears skin
overnight

Active Clearing

1 US FL OZ / 30 mL ℮

dermalogica
professional-grade skin care by The International Dermal Institute